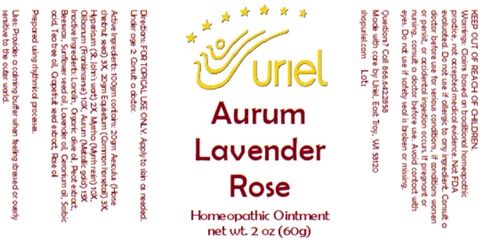 DRUG LABEL: Aurum Lavender Rose
NDC: 48951-1195 | Form: OINTMENT
Manufacturer: Uriel Pharmacy Inc.
Category: homeopathic | Type: HUMAN OTC DRUG LABEL
Date: 20250107

ACTIVE INGREDIENTS: HORSE CHESTNUT 3 [hp_X]/1 g; EQUISETUM ARVENSE TOP 3 [hp_X]/1 g; ST. JOHN'S WORT 2 [hp_X]/1 g; MYRRH 10 [hp_X]/1 g; FRANKINCENSE 10 [hp_X]/1 g; GOLD 13 [hp_X]/1 g
INACTIVE INGREDIENTS: LANOLIN; OLIVE OIL; SPHAGNUM SQUARROSUM PEAT; YELLOW WAX; SUNFLOWER OIL; LAVENDER OIL; GERANIUM OIL, ALGERIAN TYPE; SORBIC ACID; ROSE OIL; CITRUS PARADISI SEED; TEA TREE OIL

Aurum Lavender Rose

INDICATIONS AND USAGE

Directions: FOR TOPICAL USE ONLY.

DOSAGE AND ADMINISTRATION

Apply to skin as needed. Under age 2: Consult a doctor.

ACTIVE INGREDIENT

Active Ingredients: 100gm contains: 20gm Aesculus (Horse chestnut seed) 3X, 20gm Equisetum (Common horsetail) 3X; Hypericum (St. John's wort) 2X, Myrrha (Myrrh resin) 10X, Olibanum (Rubber resin from incense tree) 10X, Aurum (Metallic gold) 13X

INACTIVE INGREDIENT

Inactive Ingredients: Lanolin, Organic olive oil, Peat extract, Beeswax, Sunflower seed oil, Lavender oil, Geranium oil, Sorbic acid, Tea tree oil, Rose oil, Grapefruit seed extract

Prepared using rhythmical processes.

PURPOSE

Uses: Provides a calming buffer when feeling stressed or overly sensitive to the outer world.

KEEP OUT OF REACH OF CHILDREN.

WARNINGS

Warnings: Claims based on traditional homeopathic practice, not accepted medical evidence. Not FDA evaluated. Do not use if allergic to any ingredient. Consult a doctor before use for serious conditions, if conditions worsen or persist, or accidental ingestion occurs. If pregnant or nursing, consult a doctor before use. Avoid contact with eyes.

Questions? Call 866.642.2858
Made with care by Uriel, East Troy, WI 53120
shopuriel.com Lot: